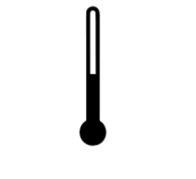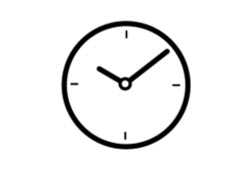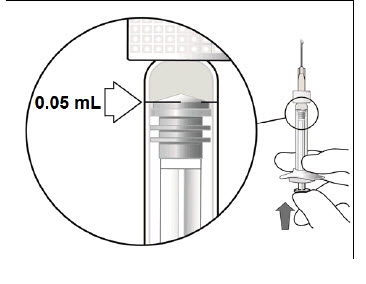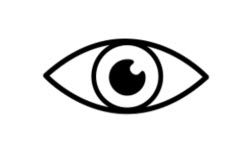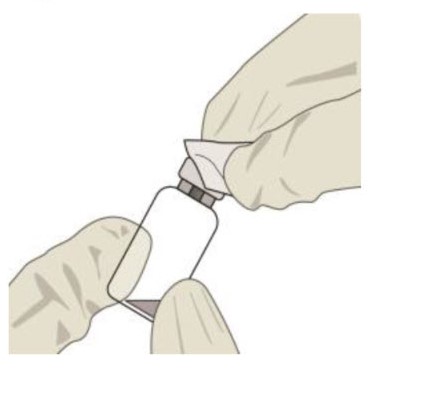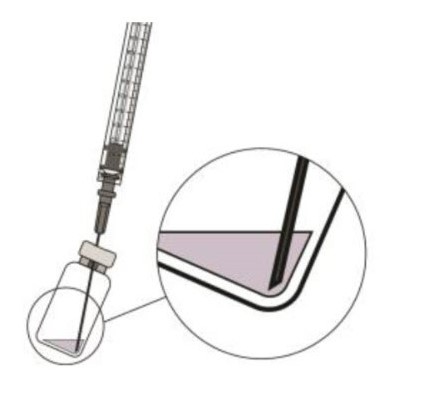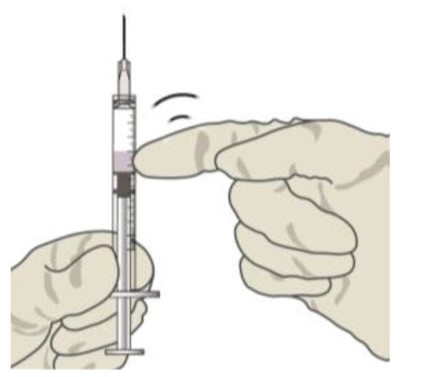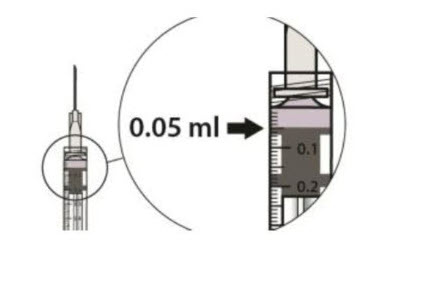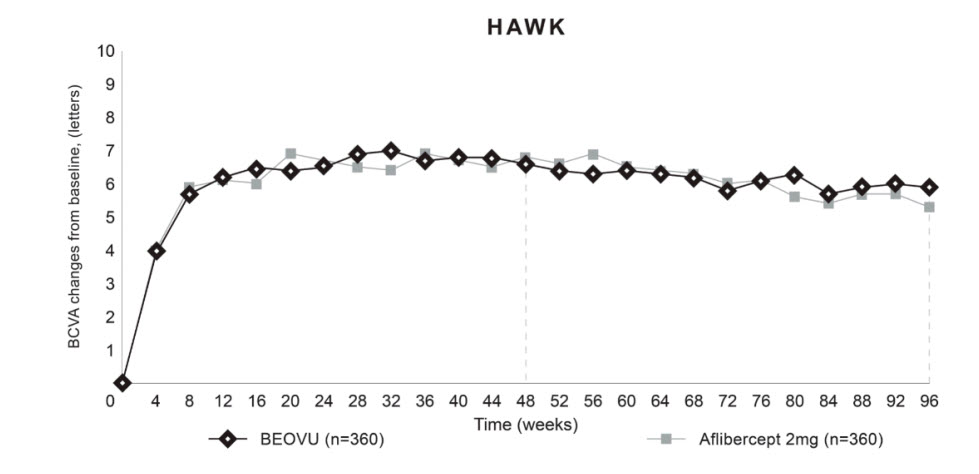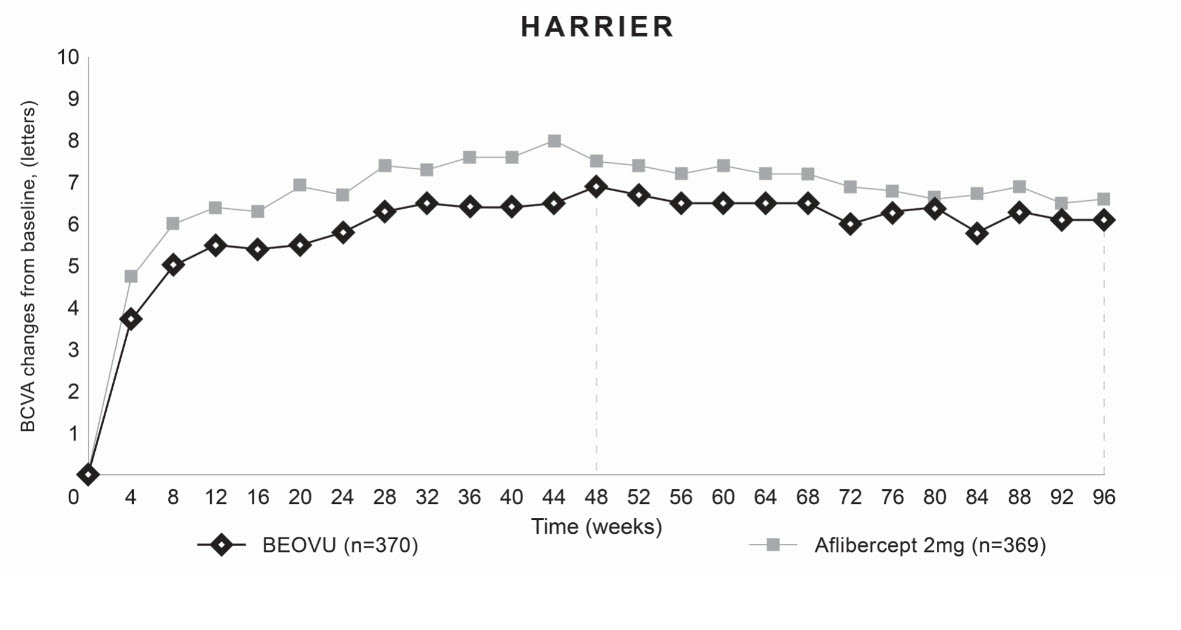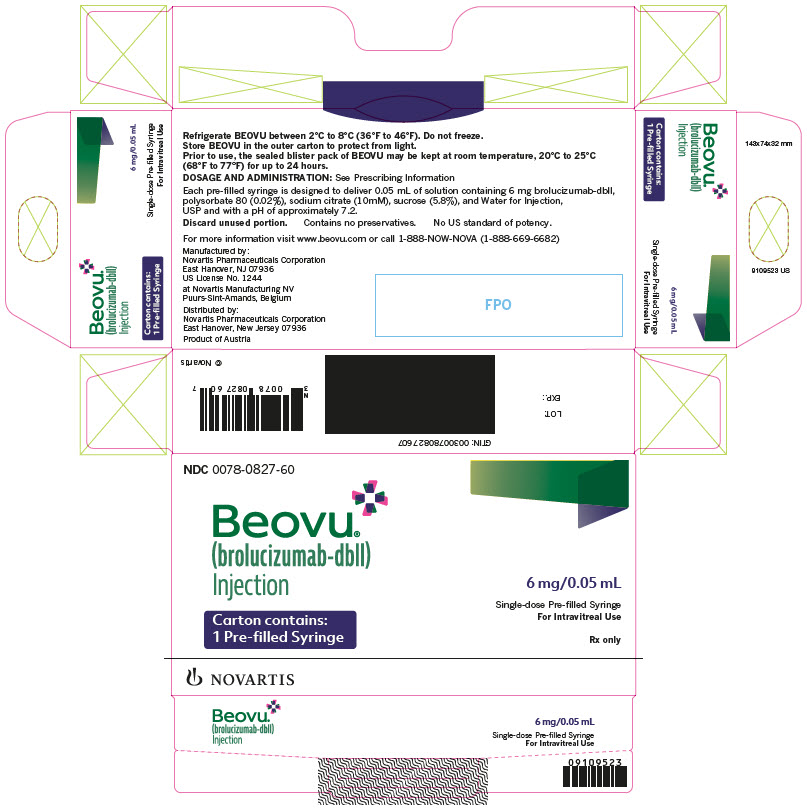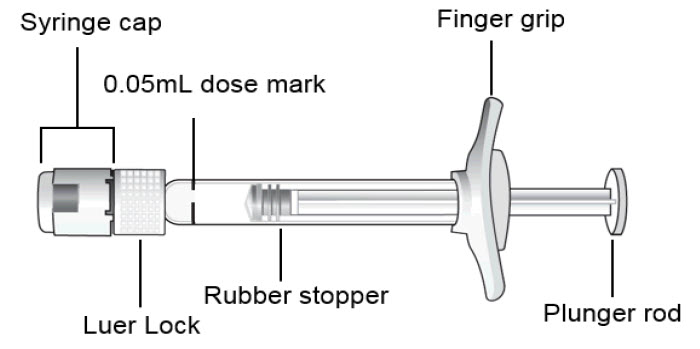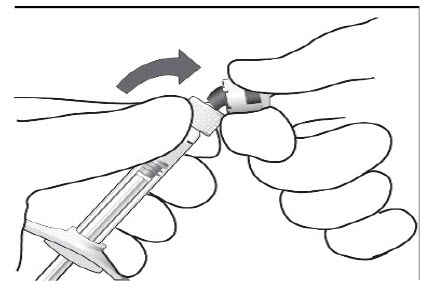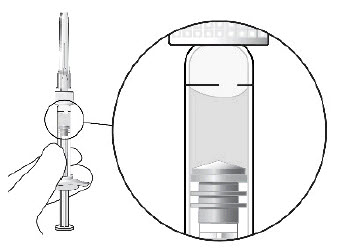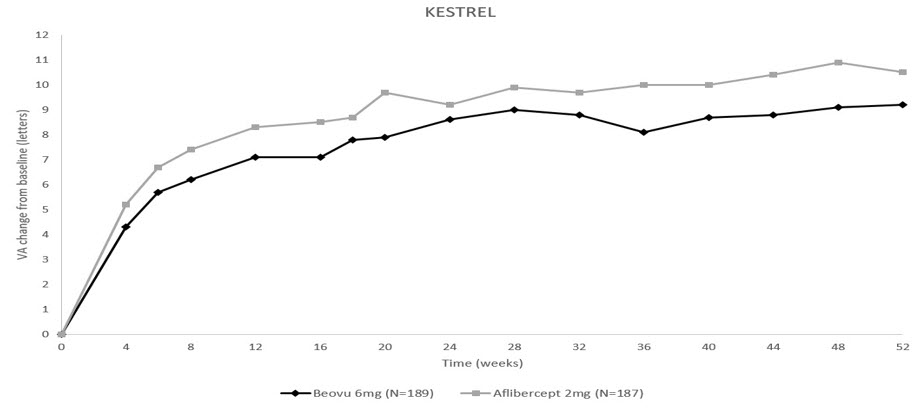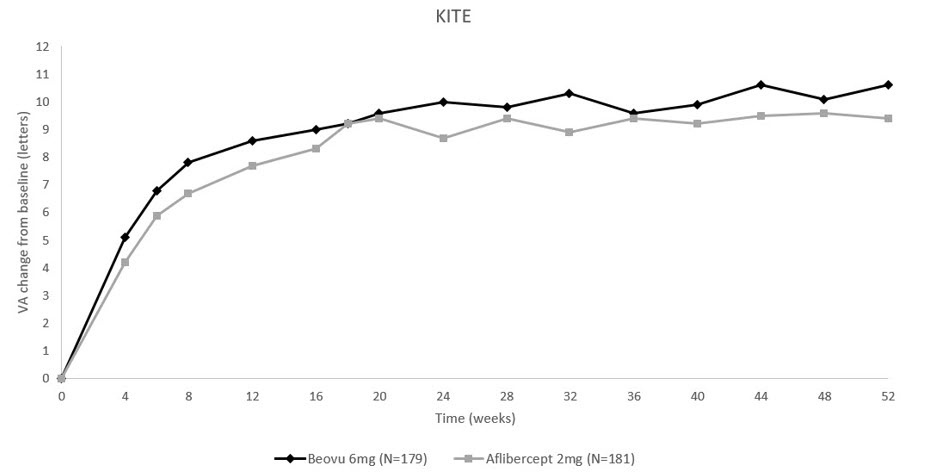 DRUG LABEL: BEOVU
NDC: 0078-0827 | Form: INJECTION, SOLUTION
Manufacturer: Novartis Pharmaceuticals Corporation
Category: prescription | Type: HUMAN PRESCRIPTION DRUG LABEL
Date: 20251103

ACTIVE INGREDIENTS: BROLUCIZUMAB 6 mg/0.05 mL
INACTIVE INGREDIENTS: SUCROSE 13.3 mg/0.05 mL; SODIUM CITRATE, UNSPECIFIED FORM 0.59 mg/0.05 mL; POLYSORBATE 80 0.05 mg/0.05 mL; SODIUM HYDROXIDE; NITROGEN; WATER

HIGHLIGHTS OF PRESCRIBING INFORMATION

These highlights do not include all the information needed to use BEOVU safely and effectively. See full prescribing information for BEOVU.
BEOVU® (brolucizumab-dbll) injection, for intravitreal use
Initial U.S. Approval: 2019

1 INDICATIONS AND USAGE

BEOVU is a human vascular endothelial growth factor (VEGF) inhibitor indicated for the treatment of:

- Neovascular (Wet) Age-Related Macular Degeneration (AMD) (1.1)
- Diabetic Macular Edema (DME) (1.2)

2 DOSAGE AND ADMINISTRATION

Neovascular (Wet) Age-Related Macular Degeneration (AMD)

- The recommended dose for BEOVU is 6 mg (0.05 mL of 120 mg/mL solution) monthly (approximately every 25-31 days) for the first three doses, followed by one dose of 6 mg (0.05 mL) every 8-12 weeks (2.2).

Diabetic Macular Edema (DME)

- The recommended dose for BEOVU is 6 mg (0.05 mL of 120 mg/mL solution) every six weeks (approximately every 39-45 days) for the first five doses, followed by one dose of 6 mg (0.05 mL of 120 mg/mL solution) every 8-12 weeks (2.3).

3 DOSAGE FORMS AND STRENGTHS

- Intravitreal injection: 6 mg/0.05 mL solution in a single-dose pre-filled syringe (3).
- Intravitreal injection: 6 mg/0.05 mL solution in a single-dose vial (3).

4 CONTRAINDICATIONS

- Ocular or Periocular Infections (4.1)
- Active Intraocular Inflammation (4.2)
- Hypersensitivity (4.3)

5 WARNINGS AND PRECAUTIONS

- Endophthalmitis and retinal detachment may occur following intravitreal injections. Patients should be instructed to report any symptoms suggestive of endophthalmitis or retinal detachment without delay (5.1).
- Retinal vasculitis and/or retinal vascular occlusion, typically in the presence of intraocular inflammation, have been reported following BEOVU injections. Patients should be instructed to report any change in vision without delay (5.2).
- Increases in intraocular pressure (IOP) have been seen within 30 minutes of an intravitreal injection (5.3).
- There is a potential risk of arterial thromboembolic events (ATE) following intravitreal use of VEGF inhibitors (5.4).

6 ADVERSE REACTIONS

The most common adverse reactions reported in patients receiving BEOVU are vision blurred, cataract, conjunctival hemorrhage, eye pain, and vitreous floaters (6.1).

To report SUSPECTED ADVERSE REACTIONS, contact Novartis Pharmaceuticals Corporation at 1-888-669-6682 or FDA at 1-800-FDA-1088 or www.fda.gov/medwatch.

FULL PRESCRIBING INFORMATION

1 INDICATIONS AND USAGE

BEOVU® is indicated for the treatment of:

2 DOSAGE AND ADMINISTRATION

2.1 General Dosing Information

For ophthalmic intravitreal injection. BEOVU must be administered by a qualified physician.

BEOVU is available packaged as follows [see How Supplied/Storage and Handling (16)]:

- Pre-filled Syringe
- Vial kit with injection components (vial, filter needle)

2.2 Neovascular (Wet) Age-Related Macular Degeneration (AMD)

The recommended dose for BEOVU is 6 mg (0.05 mL of 120 mg/mL solution) administered by intravitreal injection monthly (approximately every 25 to 31 days) for the first three doses, followed by 6 mg (0.05 mL) by intravitreal injection once every 8 to 12 weeks.

2.3 Diabetic Macular Edema (DME)

The recommended dose for BEOVU is 6 mg (0.05 mL of 120 mg/mL solution) administered by intravitreal injection every six weeks (approximately every 39-45 days) for the first five doses, followed by 6 mg (0.05 mL) by intravitreal injection once every 8-12 weeks.

2.4 Preparation for Administration – Pre-filled Syringe and Vial

Store BEOVU in the refrigerator between 2°C to 8°C (36°F to 46°F); do not freeze. Keep BEOVU in the outer carton to protect from light.

Prior to use, the unopened glass vial or sealed blister pack of BEOVU may be kept at room temperature, 20°C to 25°C (68°F to 77°F) for up to 24 hours. After opening, proceed under aseptic conditions.

BEOVU is a clear to slightly opalescent and colorless to slightly brownish-yellow solution.

BEOVU should be inspected visually upon removal from the refrigerator and prior to administration. If particulates, cloudiness, or discoloration are visible, the BEOVU must not be used.

Use aseptic technique for preparation of the intravitreal injection.

Pre-filled Syringe

The BEOVU pre-filled glass syringe is sterile and for the treatment of a single eye. It should be inspected visually prior to administration. Do not use if the packaging, or pre-filled syringe are opened, damaged, or expired [see How Supplied/Storage and Handling (16)].

STEP 1: PREPARE
Peel the lid off the blister package and, using aseptic technique, remove the sterile syringe.

STEP 2: SNAP OFF SYRINGE CAP
Snap off the syringe cap and dispose of it (see Figure 1).
Do not turn or twist the syringe cap.

Figure 1:

STEP 3: ATTACH INJECTION NEEDLE
Aseptically and firmly assemble a 30-gauge x ½ inch sterile injection needle (not included) onto the Luer lock syringe.

STEP 4: DISLODGE AIR BUBBLES
To check for air bubbles, hold the syringe with the needle pointing up. If there are any air bubbles, gently tap the syringe with your finger until the bubbles rise to the top (see Figure 2).
Carefully remove the needle cap by pulling it straight off.

Figure 2:

STEP 5: EXPEL AIR AND SET THE DOSE
Hold the syringe at eye level and carefully push the plunger until the edge below the dome of the rubber stopper is aligned with the 0.05 mL dose mark (see Figure 3). This will expel the air and the excess liquid and set the dose to the 0.05 mL dose mark. The syringe is ready for the injection.

Figure 3:

Vial

The BEOVU vial kit includes the sterile glass vial and filter needle which are sterile and for the treatment of a single eye. It should be inspected visually prior to administration. Do not use if the packaging, vial, and/or filter needle are damaged or expired [see How Supplied/Storage and Handling (16)].

STEP 1: Gather the supplies needed.

- One BEOVU vial (included)
- One sterile 5-micron blunt filter needle (18-gauge x 1½ inch, 1.2 mm x 40 mm) (included)
- One sterile 30-gauge x ½ inch injection needle (not included)
- One sterile 1 mL syringe with a 0.05 mL dose mark (not included)
- Alcohol swab (not included)

STEP 2:
Inspect the solution. If particulates, cloudiness, or discoloration are visible, discard the vial and obtain a new vial.

STEP 3:
Remove the vial cap and clean the vial septum (e.g., with alcohol swab) (see Figure 4).

Figure 4:

STEP 4:
Assemble the 5-micron filter needle (18-gauge x 1½ inch) onto a 1-mL syringe using aseptic technique.

STEP 5:
Push the filter needle into the center of the vial septum until the needle touches the bottom of the vial.

STEP 6:
To withdraw the liquid, hold the vial slightly inclined and slowly withdraw all the liquid from the vial and filter needle (see Figure 5).
Ensure that the plunger rod is drawn sufficiently back when emptying the vial in order to completely empty the filter needle.

Figure 5:

STEP 7:
Disconnect the filter needle from the syringe in an aseptic manner and dispose of it. The filter needle is not to be used for the intravitreal injection.

STEP 8:
Aseptically and firmly assemble a 30-gauge x ½ inch injection needle onto the syringe.

STEP 9:
Check for air bubbles by holding the syringe with the needle pointing up. If there are any air bubbles, gently tap the syringe with your finger until the bubbles rise to the top (see Figure 6).

Figure 6:

STEP 10:
Carefully expel the air from the syringe and adjust the dose to the 0.05 mL mark (see Figure 7).
The syringe is ready for the injection.

Figure 7:

2.5 Injection Procedure

Ensure that the injection is given immediately after preparation of the dose.

The intravitreal injection procedure must be carried out under aseptic conditions, which includes the use of surgical hand disinfection, sterile gloves, a sterile drape and a sterile eyelid speculum (or equivalent), and the availability of sterile paracentesis equipment (if required). Adequate anesthesia and a broad-spectrum topical microbicide to disinfect the periocular skin, eyelid, and ocular surface should be administered prior to the injection.

Inject slowly until the rubber stopper reaches the end of the syringe to deliver the volume of 0.05 mL. Confirm delivery of the full dose by checking that the rubber stopper has reached the end of the syringe barrel.

Immediately following the intravitreal injection, patients should be monitored for elevation in intraocular pressure (IOP). Appropriate monitoring may consist of a check for perfusion of the optic nerve head or tonometry. If required, a sterile paracentesis needle should be available.

Following intravitreal injection, patients should be instructed to report any symptoms suggestive of endophthalmitis or retinal detachment (e.g., eye pain, redness of the eye, photophobia, blurring of vision) without delay [see Patient Counseling Information (17)].

Each vial or pre-filled syringe should only be used for the treatment of a single eye. If the contralateral eye requires treatment, a new vial or pre-filled syringe should be used and the sterile field, syringe, gloves, drapes, eyelid speculum, filter, and injection needles should be changed before BEOVU is administered to the other eye.

Any unused medicinal product or waste material should be disposed of in accordance with local regulations.

3 DOSAGE FORMS AND STRENGTHS

BEOVU is a clear to slightly opalescent and colorless to slightly brownish-yellow solution available as:

- Intravitreal injection: 6 mg/0.05 mL in a single-dose pre-filled syringe.
- Intravitreal injection: 6 mg/0.05 mL in a single-dose vial.

4 CONTRAINDICATIONS

4.1 Ocular or Periocular Infections

BEOVU is contraindicated in patients with ocular or periocular infections.

4.2 Active Intraocular Inflammation

BEOVU is contraindicated in patients with active intraocular inflammation.

4.3 Hypersensitivity

BEOVU is contraindicated in patients with known hypersensitivity to brolucizumab or any of the excipients in BEOVU. Hypersensitivity reactions may manifest as rash, pruritus, urticaria, erythema, or severe intraocular inflammation.

5 WARNINGS AND PRECAUTIONS

5.1 Endophthalmitis and Retinal Detachment

Intravitreal injections, including those with BEOVU, have been associated with endophthalmitis and retinal detachment [see Contraindications (4.1) and Adverse Reactions (6.1)]. Proper aseptic injection techniques must always be used when administering BEOVU. Patients should be instructed to report any symptoms suggestive of endophthalmitis or retinal detachment without delay and should be managed appropriately [see Dosage and Administration (2.4) and Patient Counseling Information (17)].

5.2 Retinal Vasculitis and/or Retinal Vascular Occlusion

Retinal vasculitis and/or retinal vascular occlusion, typically in the presence of intraocular inflammation, have been reported with the use of BEOVU. These immune-mediated adverse events may occur following the first intravitreal injection. Discontinue treatment with BEOVU in patients who develop these events. Patients treated with BEOVU who experience intraocular inflammation may be at risk of developing retinal vasculitis and/or retinal vascular occlusion and should be closely monitored [see Contraindications (4.2) and Adverse Reactions (6.1, 6.2)]. Patients should be instructed to report any change in vision without delay.

5.3 Increase in Intraocular Pressure

Acute increases in intraocular pressure (IOP) have been seen within 30 minutes of intravitreal injection, including with BEOVU [see Adverse Reactions (6.1)]. Sustained IOP increases have also been reported. Both IOP and perfusion of the optic nerve head must be monitored and managed appropriately [see Dosage and Administration (2.4)].

5.4 Thromboembolic Events

Although there was a low rate of arterial thromboembolic events (ATEs) observed in the BEOVU clinical trials, there is a potential risk of ATEs following intravitreal use of VEGF inhibitors. Arterial thromboembolic events are defined as nonfatal stroke, nonfatal myocardial infarction, or vascular death (including deaths of unknown cause).

The ATE rate in the two controlled 96-week neovascular AMD studies (HAWK and HARRIER) during the first 96 weeks was 4.5% (33 of 730) in the pooled brolucizumab arms compared with 4.7% (34 of 729) in the pooled aflibercept arms [see Clinical Studies (14.1)].

6 ADVERSE REACTIONS

The following potentially serious adverse reactions are described elsewhere in the labeling:

- Hypersensitivity [see Contraindications (4.3)]
- Endophthalmitis and Retinal Detachment [see Warnings and Precautions (5.1)]
- Retinal Vasculitis and/or Retinal Vascular Occlusion [see Warnings and Precautions (5.2)]
- Increase in Intraocular Pressure [see Warnings and Precautions (5.3)]
- Thromboembolic Events [see Warnings and Precautions (5.4)]

6.1 Clinical Trials Experience

Because clinical trials are conducted under widely varying conditions, adverse reaction rates observed in one clinical trial of a drug cannot be directly compared with rates in the clinical trials of the same or another drug and may not reflect the rates observed in practice.

A total of 1,646 patients treated with brolucizumab constituted the safety population in four Phase 3 studies. Among these, 1,098 patients were treated with the recommended dose of 6 mg.

A total of 1,088 patients treated with brolucizumab, constituted the safety population in the two controlled neovascular AMD Phase 3 studies (HAWK and HARRIER) with a cumulative 96-week exposure to BEOVU, and 730 patients treated with the recommended dose of 6 mg [see Clinical Studies (14.1)]. A total of 558 patients treated with brolucizumab constituted the safety population in the two controlled DME Phase 3 studies (KESTREL and KITE) from baseline to week 52, including 368 patients treated with the recommended dose of 6 mg [see Clinical Studies (14.2)].

Table 1: Common Adverse Reactions (≥ 1%) in the AMD and DME Clinical Trials
 | BEOVU |  | Active Control (aflibercept)
Adverse Drug Reactions | AMD (N = 730) | DME (N = 368) | AMD (N = 729) | DME (N = 368)
Vision blurreda | 10% | 2% | 11% | 4%
Cataract | 7% | 4% | 11% | 5%
Conjunctival hemorrhage | 6% | 6% | 7% | 7%
Vitreous floaters | 5% | 3% | 3% | 2%
Eye pain | 5% | 3% | 6% | 2%
Intraocular inflammationb | 4% | 3% | 1% | 1%
Intraocular pressure increased | 4% | 2% | 5% | 1%
Retinal hemorrhage | 4% |  | 3% | 1%
Vitreous detachment | 4% | 2% | 3% | 1%
Conjunctivitis | 3% | 2% | 2% | < 1%
Retinal pigment epithelial tear | 3% |  | 1%
Corneal abrasion | 2% | 1% | 2% | 2%
Hypersensitivityc | 2% | 1% | 1% | 1%
Punctate keratitis | 1% | 1% | 2%
Retinal tear | 1% | < 1% | 1% | < 1%
Endophthalmitis | 1% | < 1% | < 1% | 1%
Blindnessd | 1% | < 1% | < 1%
Retinal artery occlusion | 1% | 1% | < 1% | < 1%
Retinal detachment | 1% |  | < 1% | 1%
Conjunctival hyperemia | 1% | < 1% | 1% | 1%
Lacrimation increased | 1% | < 1% | 1% | < 1%
Abnormal sensation in eye | 1% | < 1% | 2% | 1%
Detachment of retinal pigment epithelium | 1% |  | < 1%
Vitreous hemorrhage | < 1% | 1% | < 1% | 1%
aIncluding vision blurred, visual acuity reduced, visual acuity reduced transiently, and visual impairment.
bIncluding anterior chamber cell, anterior chamber flare, anterior chamber inflammation, chorioretinitis, eye inflammation, iridocyclitis, iritis, retinal vasculitis, retinal vascular occlusion, uveitis, vitreous haze, vitritis.
cIncluding urticaria, rash, pruritus, erythema.
dIncluding blindness, blindness transient, amaurosis, and amaurosis fugax.

In clinical trials, scleritis and episcleritis were reported (incidence < 1%).

In a clinical study (MERLIN), patients with nAMD who received BEOVU every 4-week maintenance dosing experienced a higher incidence of intraocular inflammation (including retinal vasculitis) and retinal vascular occlusion than patients who received BEOVU every 8 or 12-week maintenance dosing in the clinical studies (HAWK and HARRIER). The interval between two BEOVU doses during maintenance treatment should not be less than 8 weeks.

6.2 Immunogenicity

As with all therapeutic proteins, there is a potential for an immune response in patients treated with BEOVU. The immunogenicity of BEOVU was evaluated in serum samples. The immunogenicity data reflect the percentage of patients whose test results were considered positive for antibodies to BEOVU in immunoassays. The detection of an immune response is highly dependent on the sensitivity and specificity of the assays used, sample handling, timing of sample collection, concomitant medications, and underlying disease. For these reasons, comparison of the incidence of antibodies to BEOVU with the incidence of antibodies to other products may be misleading.

Anti-brolucizumab antibodies were detected in the pre-treatment sample of 36% to 64% of treated naive patients. After initiation of dosing, anti-brolucizumab antibodies were detected in at least one serum sample in 53% to 76% of patients treated with BEOVU. Intraocular inflammation was observed in 6% of patients with anti-brolucizumab antibodies detected during dosing with BEOVU in clinical trials. Retinal vasculitis and/or retinal vascular occlusion, typically in the presence of intraocular inflammation, are immune-mediated adverse events related to exposure to BEOVU. This treatment-emergent antibody response may develop following the first intravitreal injection. Anti-brolucizumab antibodies were not associated with an impact on clinical efficacy.

8 USE IN SPECIFIC POPULATIONS

8.1 Pregnancy

Risk Summary

There are no adequate and well-controlled studies of BEOVU administration in pregnant women. In an animal reproduction study, intravitreal administration of brolucizumab to pregnant monkeys once every 4 weeks in one eye from organogenesis to birth did not indicate any harmful effects with respect to pre- or postnatal development at 10-fold the maximum recommended human dose (MRHD) on a mg/kg basis (see Data).

Based on the anti-VEGF mechanism of action for brolucizumab [see Clinical Pharmacology (12.1)], treatment with BEOVU may pose a risk to human embryo-fetal development. BEOVU should be used during pregnancy only if the potential benefit outweighs the potential risk to the fetus.

All pregnancies have a background risk of birth defect, loss, and other adverse outcomes. The background risk of major birth defects and miscarriage for the indicated population is unknown. In the U.S. general population, the estimated background risk of major birth defects is 2% to 4% and of miscarriage is 15% to 20% of clinically recognized pregnancies.

Data

Animal Data

In an enhanced pre- and postnatal development (ePPND) study in pregnant cynomolgus monkeys, brolucizumab was administered to all animals by intravitreal (IVT) injection to one eye at doses of 3 or 6 mg once every 4 weeks until delivery. There was no impact of IVT administration of brolucizumab on embryo-fetal development, pregnancy or parturition; or on the survival, growth, or postnatal development of offspring at 6 mg/eye (10-fold the MRHD on a mg/kg basis).

VEGF inhibition has been shown to cause malformations, embryo-fetal resorption, and decreased fetal weight. VEGF also has been shown to affect follicular development, corpus luteum function, and fertility.

8.2 Lactation

Risk Summary

There is no information regarding the presence of brolucizumab in human milk, the effects of the drug on the breastfed infant, or the effects of the drug on milk production/excretion. Because many drugs are transferred in human milk and because of the potential for absorption and adverse reactions in the breastfed child, breastfeeding is not recommended during treatment and for at least one month after the last dose when stopping treatment with BEOVU.

8.3 Females and Males of Reproductive Potential

Contraception

Females

Females of reproductive potential should use highly effective contraception (methods that result in less than 1% pregnancy rates) during treatment with BEOVU and for at least one month after the last dose when stopping treatment with BEOVU.

Infertility

No studies on the effects of brolucizumab on fertility have been conducted. Based on its anti-VEGF mechanism of action, treatment with BEOVU may pose a risk to reproductive capacity.

8.4 Pediatric Use

The safety and efficacy of BEOVU in pediatric patients has not been established.

8.5 Geriatric Use

In the two Phase 3 clinical studies in AMD, approximately 90% (978/1089) of patients randomized to treatment with BEOVU were ≥ 65 years of age and approximately 60% (648/1089) were ≥ 75 years of age. In the two Phase 3 clinical studies in DME, approximately 45% (164/368) of patients randomized to treatment with BEOVU were ≥ 65 years of age and approximately 10% (37/368) were ≥ 75 years of age. No significant differences in efficacy or safety were seen with increasing age in these studies. No dosage regimen adjustment is required in patients 65 years and above.

11 DESCRIPTION

Brolucizumab-dbll is a recombinant human vascular endothelial growth factor inhibitor. Brolucizumab-dbll is a humanized monoclonal single-chain Fv (scFv) antibody fragment. Brolucizumab-dbll has a molecular weight of ~26 kilodaltons and is produced in Escherichia coli cells by recombinant DNA technology.

BEOVU (brolucizumab-dbll) injection is a sterile, clear to slightly opalescent, colorless to slightly brownish-yellow solution in a single-dose pre-filled syringe or a single-dose vial for intravitreal administration. Each single-dose pre-filled syringe and vial is designed to deliver 0.05 mL of solution containing 6 mg brolucizumab-dbll, polysorbate 80 (0.02%), sodium citrate (10 mM), sucrose (5.8%), and Water for Injection, USP and with a pH of approximately 7.2. This product does not contain an antimicrobial preservative.

12 CLINICAL PHARMACOLOGY

12.1 Mechanism of Action

Brolucizumab is a human VEGF inhibitor. Brolucizumab binds to the three major isoforms of VEGF-A (e.g., VEGF110, VEGF121, and VEGF165), thereby preventing interaction with receptors VEGFR-1 and VEGFR-2. By inhibiting VEGF-A, brolucizumab suppresses endothelial cell proliferation, neovascularization, and vascular permeability.

12.2 Pharmacodynamics

Leakage of blood and fluid from choroidal neovascularization (CNV) may cause retinal thickening or edema. Increased retinal thickness and accumulation of intraretinal fluid (IRF)/subretinal fluid (SRF), assessed by optical coherence tomography (OCT), is associated with nAMD and DME. Reductions in central retinal subfield thickness (CST) were observed across all treatment arms.

12.3 Pharmacokinetics

Following a single intravitreal dose of BEOVU to 25 AMD patients, the mean (range) serum Cmax of free brolucizumab (unbound to VEGF-A) was 49 ng/mL (9 to 548 ng/mL) and was attained at 24 hours post-dose. Brolucizumab concentrations were near or less than 0.5 ng/mL (lower limit of assay quantitation) at approximately 4 weeks after repeat dose administration and no accumulation in serum was observed in most patients.

Elimination

The estimated mean (± standard deviation) systemic half-life of brolucizumab is 4.4 days (± 2.0 days) after a single intravitreal dose.

Metabolism

Metabolism of brolucizumab has not been fully characterized. However, free brolucizumab is expected to undergo metabolism via proteolysis.

Excretion

The excretion of brolucizumab has not been fully characterized. However, free brolucizumab is expected to undergo target-mediated disposition and/or passive renal excretion.

Specific Populations

Following repeat intravitreal dose administration of BEOVU in the HAWK and HARRIER clinical studies, no differences in the systemic pharmacokinetics of brolucizumab were observed based on age (50 years and above), sex, or mild to moderate renal impairment (glomerular filtration rate (GFR) = 30 to 70 mL/min, estimated using the Modification of Diet in Renal Disease (MDRD) equation). The effect of severe renal impairment or any degree of hepatic impairment on the pharmacokinetics of BEOVU is unknown. As significant increases in serum brolucizumab exposures are not expected with intravitreal route of administration, no dosage adjustment is needed based on renal or hepatic impairment status.

Drug Interaction Studies

No studies evaluating the drug interaction potential of BEOVU have been conducted.

13 NONCLINICAL TOXICOLOGY

13.1 Carcinogenesis, Mutagenesis, Impairment of Fertility

No studies have been conducted on the carcinogenic or mutagenic potential of BEOVU. Based on the anti-VEGF mechanism of action, treatment with BEOVU may pose a risk to reproductive capacity [see Use in Specific Populations (8.3)].

14 CLINICAL STUDIES

14.1 Neovascular (Wet) Age-Related Macular Degeneration (AMD)

The safety and efficacy of BEOVU were assessed in two randomized, multi-center, double-masked, active-controlled studies (HAWK - NCT02307682 and HARRIER - NCT02434328) in patients with neovascular AMD. A total of 1,817 patients were treated in these studies for two years (1,088 on brolucizumab and 729 on control). Patient ages ranged from 50 to 97 years with a mean of 76 years.

In HAWK, patients were randomized in a 1:1:1 ratio to the following dosing regimens:

1) brolucizumab 3 mg administered every 8 or 12 weeks after the first 3 monthly doses,

2) brolucizumab 6 mg administered every 8 or 12 weeks after the first 3 monthly doses,

3) aflibercept 2 mg administered every 8 weeks after the first 3 monthly doses.

In HARRIER, patients were randomized in a 1:1 ratio to the following dosing regimens:

1) brolucizumab 6 mg administered every 8 or 12 weeks after the first 3 monthly doses,

2) aflibercept 2 mg administered every 8 weeks after the first 3 monthly doses.

In both studies, after three initial monthly doses (Week 0, 4, and 8), treating physicians decided whether to treat each individual patient on an every 8-week or 12-week dosing interval guided by visual and anatomical measures of disease activity, although the utility of these measures has not been established. Patients on 12-week dosing intervals could be changed based on the same measures to an 8-week schedule after subsequent treatment visits. Any patient placed on an 8-week schedule, remained on the 8-week dosing interval until the end of the study. Protocol-specified visits in the initial three months occurred every 28 ± 3 days followed by every 28 ± 7 days for the remainder of the studies. Baseline anatomical measures may have contributed to the regimen selection because the majority of patients on the 12-week dosing schedule at the end of the trial had less baseline macular edema and/or smaller baseline lesions.

Both studies demonstrated efficacy in the primary endpoint defined as the change from baseline in Best Corrected Visual Acuity (BCVA) at Week 48, measured by the Early Treatment Diabetic Retinopathy Study (ETDRS) Letter Score. In both studies, BEOVU treated patients had a similar mean change from baseline in BCVA as the patients treated with aflibercept 2 mg (fixed every 8 weeks). Detailed results of both studies are shown in Table 2 and Figures 8 and 9 below.

Table 2: Efficacy Outcomes at Week 48 and 96 in Phase 3 HAWK and HARRIER Studies
 |  | HAWK |  |  | HARRIER
Efficacy outcome | At week | BEOVU (n = 360) | Aflibercept 2 mg (n = 360) | Difference (95% CI) brolucizumab – aflibercept | BEOVU (n = 370) | Aflibercept 2 mg (n = 369) | Difference (95% CI) brolucizumab – aflibercept
Mean (SD) BCVA at baseline |  | 60.8 (13.7) | 60.0 (13.9) |  | 61.5 (12.6) | 60.8 (12.9)
Mean (SE) change from baseline in BCVA (measured by ETDRS letters score) | 48 96 | 6.6 (0.71) 5.9 (0.78) | 6.8 (0.71) 5.3 (0.78) | -0.2 (-2.1, 1.8) +0.5 (-1.6, 2.7) | 6.9 (0.61) 6.1 (0.73) | 7.6 (0.61) 6.6 (0.73) | -0.7 (-2.4, 1.0) -0.4 (-2.5, 1.6)
Proportion of patients who gained visual acuity (%) (≥ 15 letters of BCVA) | 48 96 | 33.6 34.2 | 25.4 27 | 8.2 (2.2, 15.0) 7.2 (1.4, 13.8) | 29.3 29.1 | 29.9 31.5 | -0.6 (-7.1, 5.8) -2.4 (-8.8, 4.1)
Proportion of patients who lost visual acuity (%) (≥ 15 letters of BCVA) | 48 96 | 6.4 8.1 | 5.5 7.4 | 0.9 (-2.7, 4.3) 0.7 (-3.6, 4.6) | 3.8 7.1 | 4.8 7.5 | -1.0 (-3.9, 2.2) -0.4 (-3.8, 3.3)
Abbreviations: BCVA, Best Corrected Visual Acuity; missing data are imputed using last observation carried forward (LOCF) method; ETDRS, Early Treatment Diabetic Retinopathy Study; SE, standard error.

Figure 8: Mean Change in Visual Acuity From Baseline to Week 96 in HAWK

Figure 9: Mean Change in Visual Acuity From Baseline to Week 96 in HARRIER

Through Week 48, 56% (HAWK) and 51% (HARRIER) of patients remained on BEOVU every 12 weeks. The proportion of patients who were maintained on every 12-week dosing through Week 96 was 45% and 39% in HAWK and HARRIER, respectively. The probability of remaining on every 12-week dosing from Week 20 to Week 48 was 85% and 82%, and from Week 48 to Week 96 was 82% and 75% in HAWK and HARRIER, respectively.

Treatment effects in evaluable subgroups (e.g., age, gender, race, baseline visual acuity) in each study were generally consistent with the results in the overall populations.

14.2 Diabetic Macular Edema (DME)

The safety and efficacy of BEOVU were assessed in two randomized, multi-center, double-masked, active controlled studies (KESTREL – NCT03481634 and KITE - NCT03481660) in patients with DME. A total of 926 patients were treated in these studies for 1 year (558 on brolucizumab and 368 on aflibercept 2 mg). Patient ages ranged from 23 to 87 years with a mean of 63 years.

In KESTREL, patients were randomized in a 1:1:1 ratio to the following dosing regimens:

1) brolucizumab 6 mg administered once every 6 weeks for first 5 doses, followed by brolucizumab 6 mg every 8 or 12 weeks.

2) brolucizumab 3 mg administered once every 6 weeks for first 5 doses, followed by brolucizumab 3 mg every 8 or 12 weeks.

3) aflibercept 2 mg administered once every 4 weeks for first 5 doses, followed by aflibercept 2 mg every 8 weeks.

In KITE, patients were randomized in a 1:1 ratio to the following dosing regimens:

1) brolucizumab 6 mg administered once every 6 weeks for first 5 doses, followed by brolucizumab 6 mg every 8 or 12 weeks.

2) aflibercept 2 mg administered once every 4 weeks for first 5 doses, followed by aflibercept 2 mg every 8 weeks.

In both studies, after the first five doses (Weeks 0, 6, 12, 18, and 24), brolucizumab patients were treated every 12 weeks, with the option of adjusting to an every 8-week dosing interval based on disease activity. Disease activity was assessed by changes in visual acuity and/or anatomical parameters, including CST and/or presence of IRF/SRF although the utility of the specific action parameters used has not been established. Disease activity was assessed by a physician during the first 12-week interval (at Weeks 32 and 36) and at each subsequent scheduled 12-week treatment visit. Patients who showed disease activity at any of these visits were adjusted to an every 8 week treatment interval. The comparator aflibercept was administered every 8 weeks after the first 5 monthly doses.

The primary efficacy endpoint for both studies was the change from baseline to Week 52 in Best Corrected Visual Acuity (BCVA) as measured by the Early Treatment Diabetic Retinopathy Study (ETDRS) Letter Score with the primary objective being to demonstrate non-inferiority of BEOVU vs. aflibercept 2 mg. In both studies, BEOVU was non-inferior to aflibercept 2 mg for the change in BCVA from baseline to Week 52 and the change from baseline over the period Week 40 through Week 52.

After 5 initial q6w loading doses, the patients in the BEOVU arm could have received between the minimum of 2 and maximum of 3 additional injections through Week 52. At Week 52, the median number of injections given over 12 months was 7 in patients treated with BEOVU.

Through Week 52, 55% (KESTREL) and 50% (KITE) of patients remained on BEOVU every 12 weeks. The probability of remaining on every 12-week dosing from Week 36 to Week 52 was 88% and 95% in KESTREL and KITE, respectively.

Results of both studies are shown in Table 3 and Figures 10 and 11 below.

Table 3: Efficacy Outcomes at Week 52 in Phase 3 - KESTREL and KITE Studies
 |  | KESTREL |  |  | KITE
Efficacy outcome | At Week | BEOVU (n = 189) | aflibercept 2 mg (n = 187) | Difference (95% CI) BEOVU – aflibercept | BEOVU (n = 179) | aflibercept 2 mg (n = 181) | Difference (95% CI) BEOVU – aflibercept
Change from baseline in BCVA (measured by ETDRS letters score) – LS mean (SE) | 52 40-52 | 9.2 (0.57) 9.0 (0.53) | 10.5 (0.57) 10.5 (0.53) | -1.3 (-2.9, 0.3) -1.5 (-3.0, 0.0) | 10.6 (0.66) 10.3 (0.62) | 9.4 (0.66) 9.4 (0.62) | 1.2 (-0.6, 3.1) 0.9 (-0.9, 2.6)
BCVA: Best Corrected Visual Acuity; BCVA assessments after start of alternative DME treatment in the study eye were censored and replaced by the last value prior to start of this alternative treatment.

Figure 10: Mean Change in Visual Acuity From Baseline to Week 52 in KESTREL

Figure 11: Mean Change in Visual Acuity From Baseline to Week 52 in KITE

Treatment effects in evaluable subgroups (i.e., age, gender, baseline HbA1c, baseline visual acuity, baseline central subfield thickness, DME lesion type, duration of DME since diagnosis, retinal fluid status) in each study were generally consistent with the results in the overall population.

In both studies, BEOVU demonstrated a significant reduction from baseline in CST starting at Week 4 and continuing up to Week 52.

16 HOW SUPPLIED/STORAGE AND HANDLING

16.1 How Supplied

BEOVU (brolucizumab-dbll) injection is supplied as a clear to slightly opalescent and colorless to slightly brownish-yellow solution in a single-dose pre-filled syringe and a single-dose vial.

Each pre-filled syringe or vial is for the treatment of a single eye. BEOVU is supplied in the following presentations [see Dosage and Administration (2.3)].

NDC NUMBER | CARTON TYPE | CARTON CONTENTS
0078-0827-60 | Pre-filled Syringe | one sealed blister pack containing one BEOVU 6 mg/0.05 mL single-dose pre-filled syringe one Prescribing Information
0078-0827-61 | Vial Kit with Injection Components | one BEOVU 6 mg/0.05 mL single-dose vial one 18-gauge x 1½ inch, 1.2 mm x 40 mm, 5-micron, filter needle for withdrawal of the contents one Prescribing Information

16.2 Storage and Handling

Refrigerate BEOVU between 2°C to 8°C (36°F to 46°F). Do not freeze. Store BEOVU in the outer carton to protect from light.

Prior to use, the unopened glass vial or sealed blister pack of BEOVU may be kept at room temperature, 20°C to 25°C (68°F to 77°F) for up to 24 hours.

17 PATIENT COUNSELING INFORMATION

Advise patients that in the days following BEOVU administration, patients are at risk of developing endophthalmitis, retinal detachment, retinal vasculitis and/or retinal vascular occlusion. If the eye becomes red, sensitive to light, painful, or if a patient develops any change in vision, instruct the patient to seek immediate care from an ophthalmologist [see Warnings and Precautions (5.1, 5.2)].

Patients may experience temporary visual disturbances after an intravitreal injection with BEOVU and the associated eye examination [see Adverse Reactions (6.1)]. Advise patients not to drive or use machinery until visual function has recovered sufficiently.

Manufactured by:
Novartis Pharmaceuticals Corporation
East Hanover, New Jersey 07936
U.S. License Number: 1244

© Novartis

T2024-60

PRINCIPAL DISPLAY PANEL

NDC 0078-0827-60

Beovu®

(brolucizumab-dbll)
Injection

6 mg/0.05 mL

Single-dose Pre-filled Syringe

For Intravitreal Use

Carton contains:

1 Pre-filled Syringe

Rx only

NOVARTIS